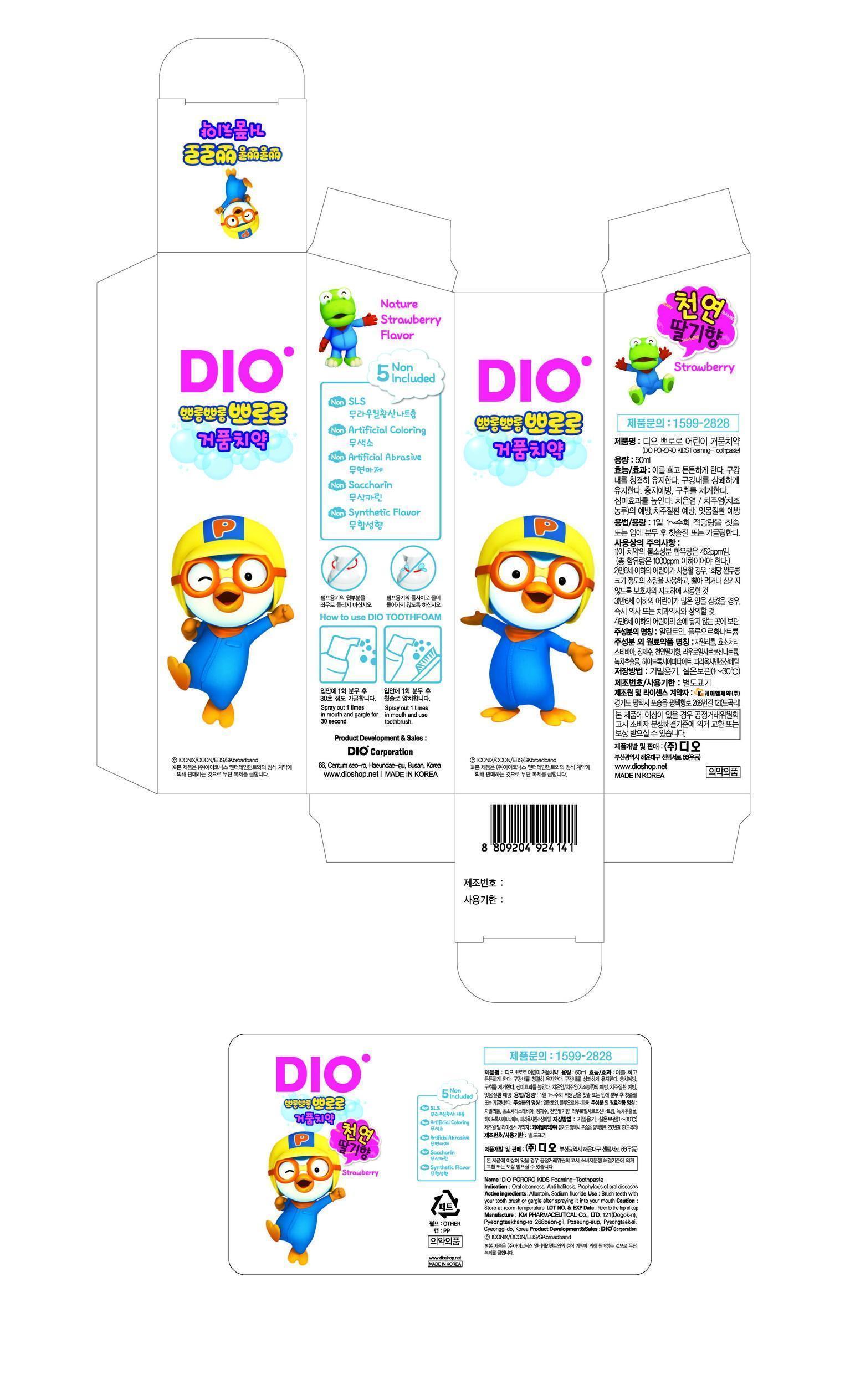 DRUG LABEL: DIO PORORO KIDS FOAMING
NDC: 75902-3001 | Form: PASTE, DENTIFRICE
Manufacturer: Dio Corporation
Category: otc | Type: HUMAN OTC DRUG LABEL
Date: 20170601

ACTIVE INGREDIENTS: SODIUM FLUORIDE 0.1 g/100 mL; ALLANTOIN 0.05 g/100 mL
INACTIVE INGREDIENTS: XYLITOL; METHYLPARABEN; WATER

Drug Facts

ACTIVE INGREDIENT

sodium fluoride, allantoin

INACTIVE INGREDIENT

xylityl, glucosyl stevia, sodium lauroyl sarcosinate, hydroxyapatite, methylparaben, natural strawberry flavor, camellia sinensis leaf ext, water

PURPOSE

for dental care

keep out of reach of the children

INDICATIONS AND USAGE

spray out 1 time in mouth and gargle for 30 seconds
spray out 1 time in mouth and use toothbrush

WARNINGS

store at room temperature

DOSAGE AND ADMINISTRATION

for dental use only